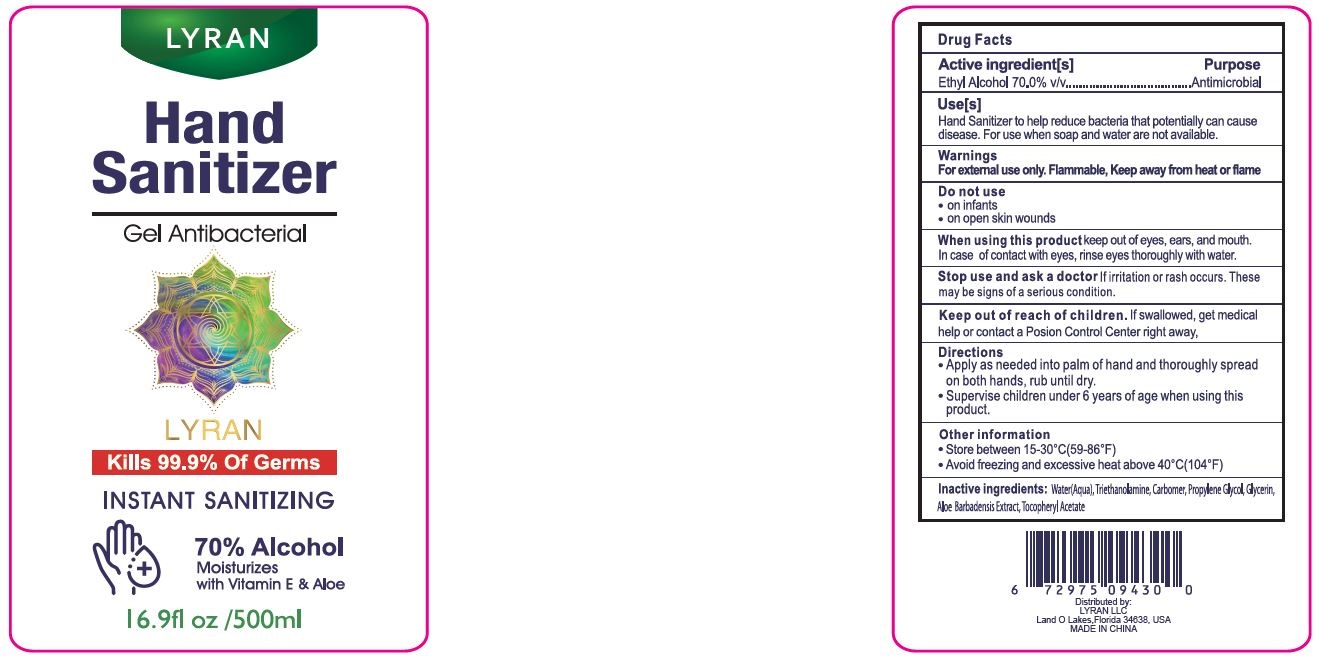 DRUG LABEL: Lyran Hand Sanitizer
NDC: 75749-008 | Form: GEL
Manufacturer: Ningbo Pretty Tourism Manufacturer Co. Ltd.
Category: otc | Type: HUMAN OTC DRUG LABEL
Date: 20200511

ACTIVE INGREDIENTS: ALCOHOL 70 mL/100 mL
INACTIVE INGREDIENTS: TROLAMINE; PROPYLENE GLYCOL; ALOE VERA LEAF; GLYCERIN; WATER; ALPHA-TOCOPHEROL ACETATE; CARBOMER HOMOPOLYMER, UNSPECIFIED TYPE

Lyran Hand Sanitizer PET bottle w/ pump top

Active Ingredient(s)

Ethyl Alcohol 70% Purpose: Antimicrobial

Purpose

Antimicrobial

Uses

Use(s)

Hand Sanitizer to help reduce bacteria that potentially can cause disease. For use when soap and water are not available.

Warnings

For external use only. Flammable, keep away from heat and flame.

Do not use

- on infants
- on open skin wounds

- Stop use and ask a doctor if irritation or rash occurs. These may be signs of a serious condition

Keep out of reach of children. If swallowed, get medical help or contact a Poison Control Center right away.

Directions

- Apply as needed into palm of hand and thoroughly spread on both hands, rub until dry.
- Supervise children under 6 years of age when using this product

Other information

- Store between 15-30C (59-86F)
- Avoid freezing and excessive heat above 40C (104F)

Inactive ingredients

Water (aqua), Triethanolamine, Carbomer, Propylene Glycol, Glycerin, Aloe Barbadensis Extract, Tocopheryl Acetate

WHEN USING

keep out of eyes, ears, and mouth. In case of contact with eyes, rinse eyes thoroughly with water.